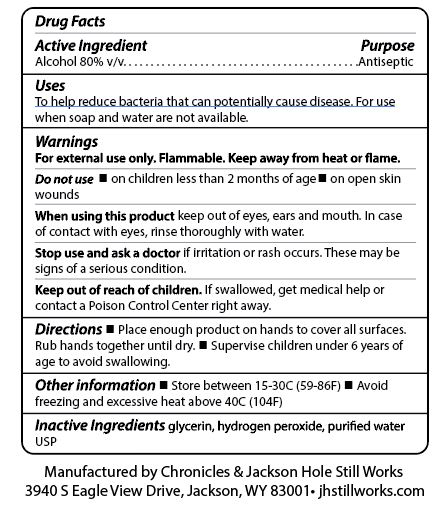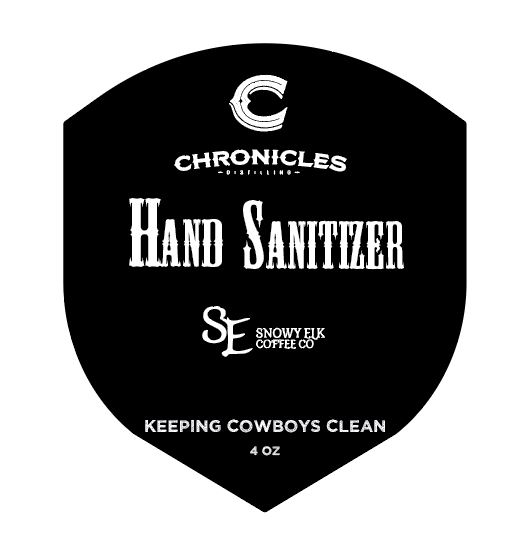 DRUG LABEL: Chronicles Distilling Hand Sanitizer
NDC: 74732-001 | Form: LIQUID
Manufacturer: Chronicles Distilling
Category: otc | Type: HUMAN OTC DRUG LABEL
Date: 20200330

ACTIVE INGREDIENTS: ALCOHOL 8333 mL/10000 mL
INACTIVE INGREDIENTS: GLYCEROL FORMAL 145 mL/10000 mL; HYDROGEN PEROXIDE 417 mL/10000 mL; WATER 1105 mL/10000 mL

Active Ingredient and Back Label

Drug Facts

Active Ingredient Purpose

Alcohol 80% v/v.........................................Antiseptic

Purpose Section

Uses

To help reduce bacteria that can potentially cause disease. For use when soap and water are not available.

Warnings

For external use only. Flammable. Keep away from heat or flame.

Do not use

- in children less than 2 months of age
- on open skin wounds

When using this product

keep out of eyes, ears, and mouth. In case of contact with eyes, rinse thoroughly with water.

Stop use and ask a doctor

if irritation or rash occurs. These may be signs of a serious condition.

Keep out of reach of children

If swallowed, get medical help or contact a Poison Control Center right away.

Directions

- Place enough product on hands to cover all surfaces. Rub hands together until dry.
- Supervise children under 6 years of age to avoid swallowing.

Other Information

- Store between 15-30C (59-86F)
- Avoid freezing and excessive heat above 40C (104F)

Inactive Ingredients

glycerin, hydrogen peroxide, purified water USP

Dosage & Administration

Directions

- Place enough hand sanitizer to cover all surfaces. Rub hands together until dry.
- Supervise children under 6 years of age to avoid swallowing.

Warnings Section

Warnings

For external use only. Flammable. Keep away from heat or flame.

Do not use

- in children less than 2 months of age
- on open skin wounds

When using this product keep out of eyes, ears, and mouth. In case of contact with eyes, rinse thoroughly with water.

Stop use and ask a doctor if irritation or rash occurs. These may be signs of a serious condition.

Keep out of reach of children. If swallowed, get medical help or contact a Poison Control Center right away.

Indications & Usage

Uses

To help reduce bacteria that can potentially cause disease. For use when soap and water are not available.

Directions

- Place enough product on hands to cover all surfaces. Rub hands together until dry.
- Supervise children under 6 years of age to avoid swallowing.

Principle display panel & Front Label

(Chronicles Distilling Logo)

Hand Sanitizer

(Snowy Elk Coffee Co. Logo)

KEEPING COWBOYS CLEAN

4 OZ